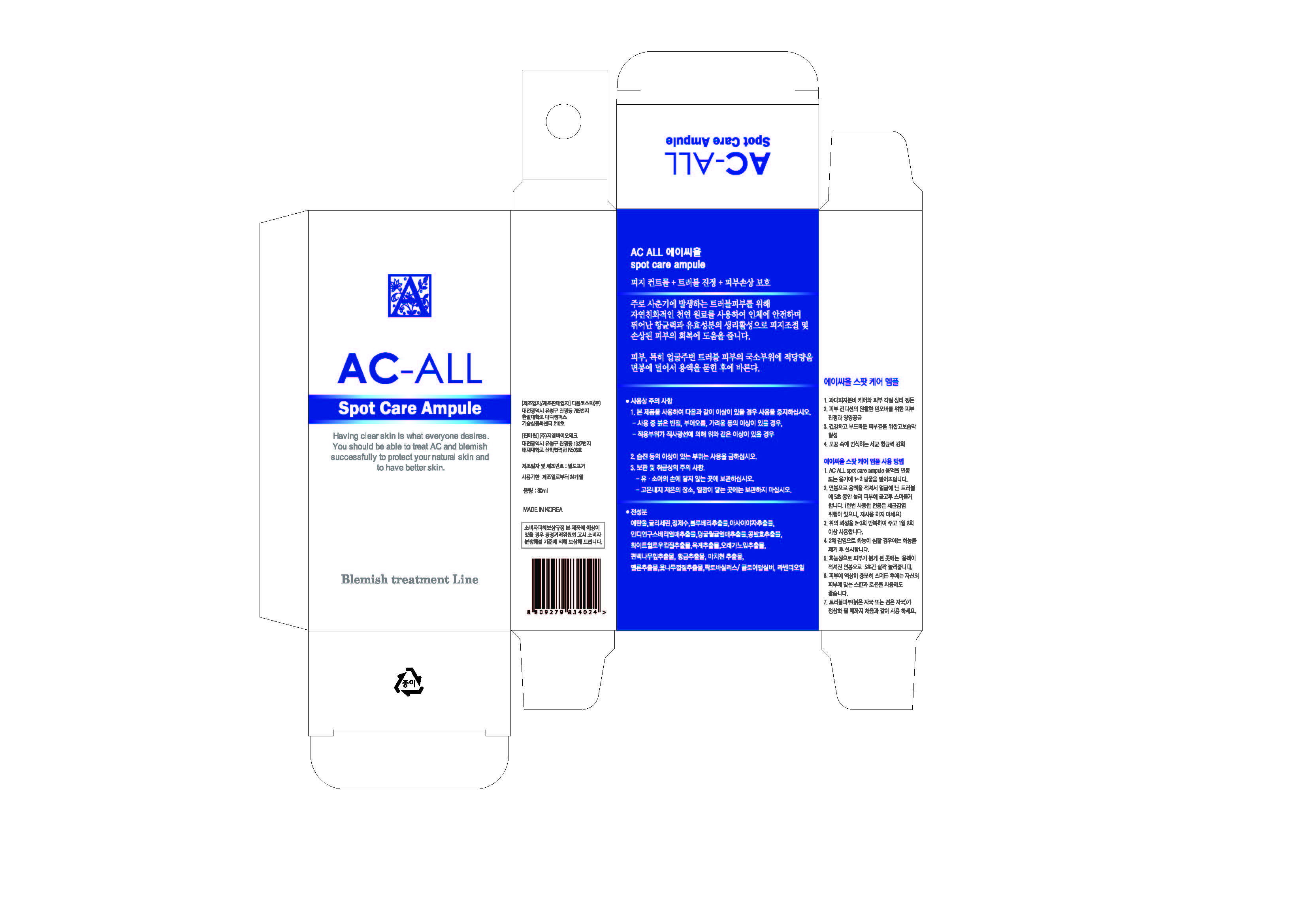 DRUG LABEL: AC ALL
NDC: 69224-2001 | Form: LIQUID
Manufacturer: GL BioTech 
Category: otc | Type: HUMAN OTC DRUG LABEL
Date: 20141017

ACTIVE INGREDIENTS: GLYCERIN 2 g/100 mL
INACTIVE INGREDIENTS: WATER; ALCOHOL

Drug Facts

ACTIVE INGREDIENT

glycerin

INACTIVE INGREDIENT

blueberry ext, assai ext, indian gooseberry fruit ext, cranberry fruit ext, melon ext, rhus tree bark ext, lactobacillus, colloidal silver, lavender oil, etc

PURPOSE

skin protection
excellent antimicrobial
safe for human body

keep out or reach of the children

INDICATIONS AND USAGE

1. Put 1-2 drops of AC ALL spot care ampule liquid on cotton bud or a vessel.
2. Place watery cotton bud on the skin and gently push for 5 minutes until absorbed.
3. Repeat 1 and 2 for 2-3 times, and 2 times a day.
4. When suppuration has occurred as a secondary infection, remove it before use.
5. Put a cotton swab dipped into the ampule lightly on the reddened spot for 5 seconds.
6. Use lotions after the liquid is fully absorbed on skin.
7. Trouble spots will disappear in 2-3 days, and generally skin will be improved in 1-2
months.
8. Use repetitively on troubled skin (Red or black marks) until the skin condition became
better.(Do not reuse the cotton bud due to the risk of bacterial infection.)

WARNINGS

- avoid direct sun exposure, keep it refrigerated or in cooler places
- do not eat

DOSAGE AND ADMINISTRATION

for exernal use only